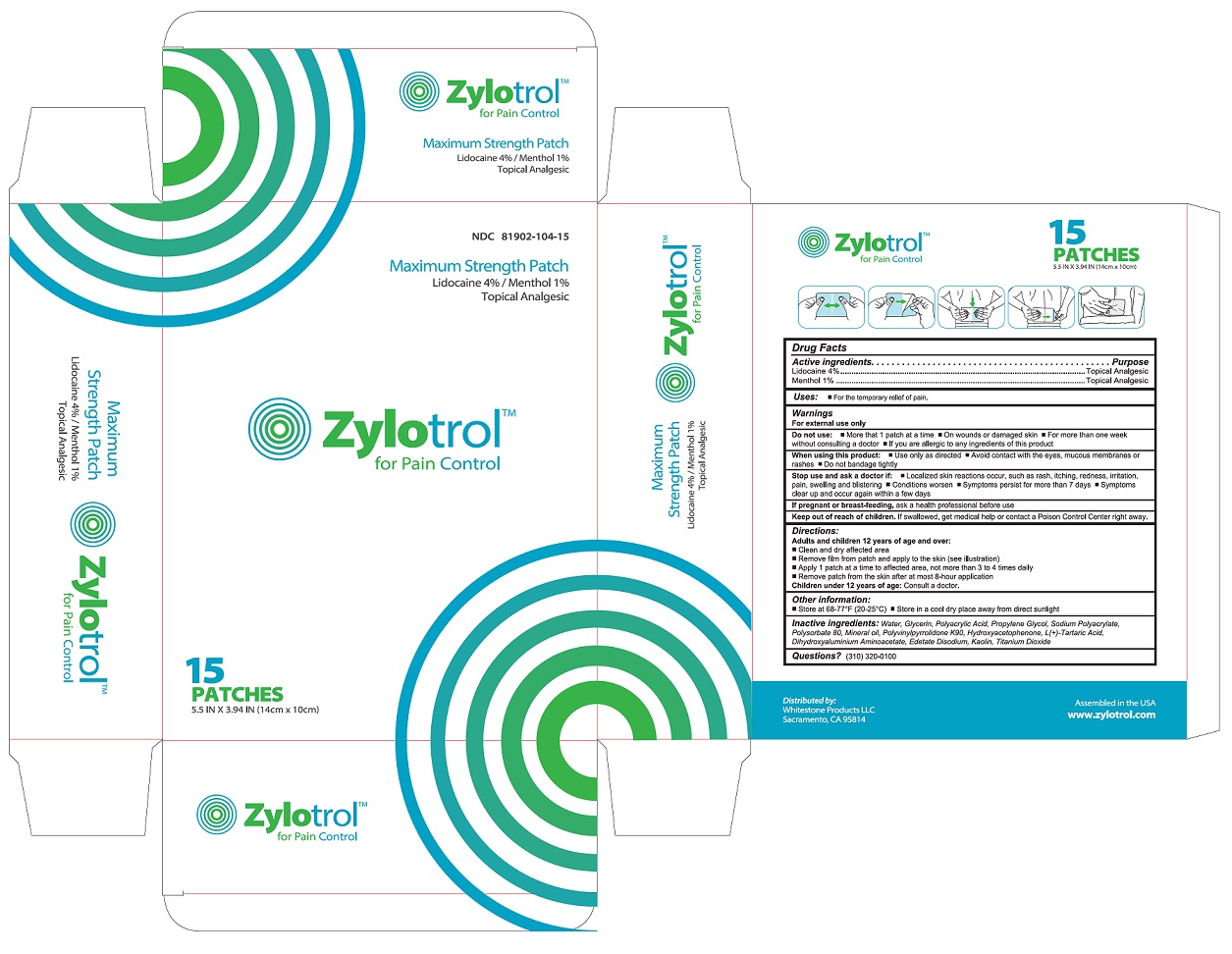 DRUG LABEL: ZYLOTROL MAXIMUM PAIN
NDC: 81902-104 | Form: PATCH
Manufacturer: Whitestone Products LLC
Category: otc | Type: HUMAN OTC DRUG LABEL
Date: 20231021

ACTIVE INGREDIENTS: MENTHOL 0.03 g/3 g; LIDOCAINE 0.12 g/3 g
INACTIVE INGREDIENTS: KAOLIN; TARTARIC ACID; WATER; DIHYDROXYALUMINUM AMINOACETATE ANHYDROUS; PROPYLENE GLYCOL; POLYACRYLIC ACID (250000 MW); SODIUM POLYACRYLATE (2500000 MW); TITANIUM DIOXIDE; MINERAL OIL; POLYSORBATE 80; GLYCERIN; EDETATE DISODIUM; POVIDONE K90; HYDROXYACETOPHENONE

ZYLOTROL MAXIMUM PAIN PATCH

Active Ingredients

Lidocaine 4% w/w

Menthol 1% w/w

Purposes

Topical analgesic

Topical analgesic

Uses

For the temporary relief of pain.

Warnings

For external use only

Do not use:

- More than 1 patch at a time
- On wounds or damaged skin
- For more than one week without consulting a doctor
- If you are allergic to any ingredients of this product

When using this product:

- Use only as directed
- Avoid contact with the eyes, mucous membranes or rashes
- Do not bandage tightly

Stop use and ask a doctor if:

- Localized skin reactions occur, such as rash, itching, redness, irritation, pain, swelling and blistering
- Condition worsen
- Symptoms persist for more than 7 days
- Symptoms clear up and occur again within a few days

If pregnant or breast-feeding,

Ask a health professional before use

Keep out of reach of children.

If swallowed, get medical help or contact a Poison Control Center right away

Directions

Adult and children 12 years of age and over:

- Clean and dry affected area
- Remove ﬁlm from patch and apply to the skin (see illustration)
- Apply 1 patch at a time to affected area, not more than 3 to 4 times daily
- Remove patch from the skin after at most 8-hour application

Children under 12 years of age: Consult a doctor

Other information

- Store at 68-77℉ (20-25℃)
- Store in a cool dry place away from direct sunlight

Inactive Ingredients

Water, Glycerin, Polyacrylic Acid, Propylene Glycol, Sodium Polyacrylate, Polysorbate 80, Mineral oil, Polyvinylpyrrolidone K90, Hydroxyacetophenone, L(+)-Tartaric Acid, Dihydroxyaluminium Aminoacetate, Edetate Disodium, Kaolin, Titanium Dioxide

Questions?

(310) 320-0100